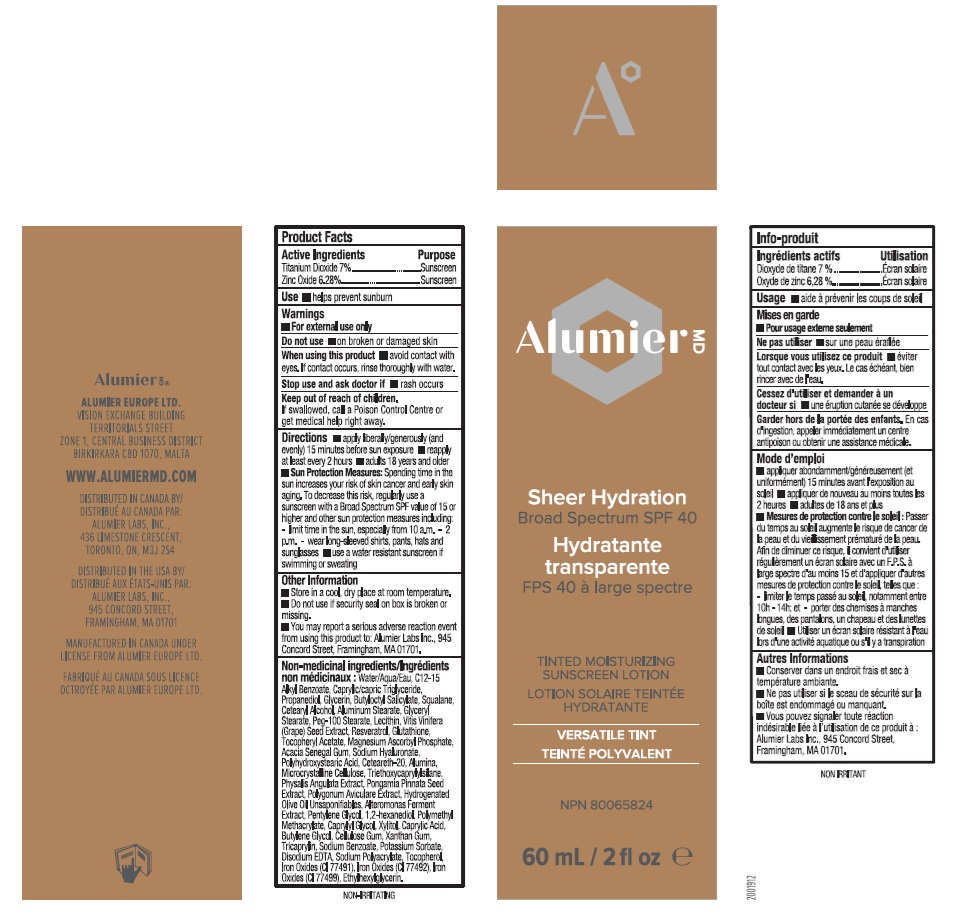 DRUG LABEL: Alumier MD Sheer Hydration Tinted Moisturizing Sunscreen
NDC: 69473-010 | Form: LOTION
Manufacturer: Alumier Labs
Category: otc | Type: HUMAN OTC DRUG LABEL
Date: 20241203

ACTIVE INGREDIENTS: ZINC OXIDE 62.8 mg/1 mL; TITANIUM DIOXIDE 70 mg/1 mL
INACTIVE INGREDIENTS: CAPRYLIC ACID; SODIUM POLYACRYLATE (2500000 MW); HYDROGENATED OLIVE OIL UNSAPONIFIABLES; POTASSIUM SORBATE; BUTYLENE GLYCOL; PHYSALIS ANGULATA; CAPRYLYL GLYCOL; PENTYLENE GLYCOL; XYLITOL; FERRIC OXIDE RED; FERRIC OXIDE YELLOW; LECITHIN, SOYBEAN; MEDIUM-CHAIN TRIGLYCERIDES; ALUMINUM MONOSTEARATE; TRIETHOXYCAPRYLYLSILANE; WATER; CETOSTEARYL ALCOHOL; GLYCERYL MONOSTEARATE; PEG-100 STEARATE; ACACIA; POLYOXYL 20 CETOSTEARYL ETHER; ALUMINUM OXIDE; XANTHAN GUM; 1,2-HEXANEDIOL; ALKYL (C12-15) BENZOATE; PROPANEDIOL; GLUTATHIONE; MAGNESIUM ASCORBYL PHOSPHATE; MICROCRYSTALLINE CELLULOSE; EDETATE DISODIUM; CARBOXYMETHYLCELLULOSE SODIUM, UNSPECIFIED FORM; TRICAPRYLIN; ETHYLHEXYLGLYCERIN; SODIUM BENZOATE; BUTYLOCTYL SALICYLATE; GLYCERIN; VITIS VINIFERA SEED; RESVERATROL; .ALPHA.-TOCOPHEROL ACETATE; POLYHYDROXYSTEARIC ACID (2300 MW); FERROSOFERRIC OXIDE; SQUALANE; POLYGONUM AVICULARE WHOLE; POLY(METHYL METHACRYLATE; 450000 MW); TOCOPHEROL; HYALURONATE SODIUM; PONGAMIA PINNATA SEED EXTRACT

Alumier MD Sheer Hydration Tinted Moisturizing Sunscreen

Active Ingredients

Titanium Dioxide 7%

Zinc Oxide 6.28%

Purpose

Sunscreen

Use

- helps prevent sunburn

Warnings

- For external use only.

Do not use

- on broken or damaged skin

When using this product

- avoid contact with eyes. If contact occurs, rinse thoroughly with water.

Stop use and ask a doctor if

- rash occurs

Keep out of reach of children.

If swallowed, call a Poison Control Centre or get medical help right away.

Directions

- apply liberally/generously (and evenly) 15 minutes before sun exposure
- reapply at least every 2 hours
- adults 18 years and older
- Sun Protection Measures: Spending time in the sun increases your risk of skin cancer and early skin aging. To decrease this risk, regularly use a sunscreen with a Broad Spectrum SPF value of 15 or higher and other sun protection measures including: - limit time in the sun, especially from 10 a.m.-2 p.m. - wear long-sleeved shirts, pants, hats and sunglasses
- use a water resistant sunscreen if swimming or sweating

Other Information

- Store in a cool, dry place at room temperature.
- Do not use if security seal on box is broken or missing.
- You may report a serious adverse reaction event from using this product to: Alumier Labs Inc., 945 Concord Street, Framingham, MA 01701

Non-medicinal ingredients

Water/Aqua/Eau, C12-15 Alkyl Benzoate, Caprylic/Capric Triglyceride, Propanediol, Glycerin, Butyloctyl Salicylate, Squalane, Cetearyl Alcohol, Aluminium Stearate, Glyceryl Stearate, Peg-100 Stearate, Lecithin, Vitis Vinifera (Grape) Seed Extract, Resveratrol, Glutathione, Tocopheryl Acetate, Magnesium Ascorbyl Phosphate, Acacia Senegal Gum, Sodium Hyaluronate, Polyhydroxystearic Acid, Ceteareth-20, Alumina, Microcrystalline Cellulose, Triethoxycaprylylsilane, Physalis Angulata Extract, Pongamia Pinnata Seed Extract, Polygonum Aviculare Extract, Hydrogenated Olive Oil Unsaponifiables, Alteromonas Ferment Extract, Pentylene Glycol, 1,2-hexanediol, Polymethyl Methacrylate, Caprylyl Glycol, Xylitol, Caprylic Acid, Butylene Glycol, Cellulose Gum, Xanthan Gum, Tricaprylin, Sodium Benzoate, Potassium Sorbate, Disodium EDTA, Sodium Polyacrylate, Tocopherol, Iron Oxides (CI 77491), Iron Oxides (CI 77492), Iron Oxides (CI 77499), Ethylhexylglycerin.